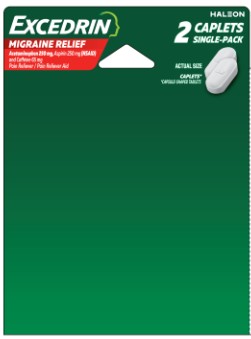 DRUG LABEL: Excedrin
NDC: 85237-1871 | Form: TABLET, FILM COATED
Manufacturer: Select Consumer Group
Category: otc | Type: HUMAN OTC DRUG LABEL
Date: 20251227

ACTIVE INGREDIENTS: ACETAMINOPHEN 250 mg/1 1; ASPIRIN 250 mg/1 1; CAFFEINE 65 mg/1 1
INACTIVE INGREDIENTS: BENZOIC ACID; CARNAUBA WAX; FD&C BLUE NO. 1; HYPROMELLOSE, UNSPECIFIED; LIGHT MINERAL OIL; HYDROXYPROPYL CELLULOSE, UNSPECIFIED; MICROCRYSTALLINE CELLULOSE; POLYSORBATE 20; POVIDONE, UNSPECIFIED; PROPYLENE GLYCOL; DIMETHICONE, UNSPECIFIED; SORBITAN MONOLAURATE; STEARIC ACID; TITANIUM DIOXIDE

Drug Facts

Active ingredients (in each caplet)

Acetaminophen 250 mg

Aspirin 250 mg (NSAID*)

Caffeine 65 mg
*nonsteroidal anti-inflammatory drug

Purposes

Pain reliever
Pain reliever
Pain reliever aid

Use

- treats migraine

Warnings

Reye’s syndrome:Children and teenagers who have or are recovering from chicken pox or flu-like symptoms should not use this product. When using this product, if changes in behavior with nausea and vomiting occur, consult a doctor because these symptoms could be an early sign of Reye’s
syndrome, a rare but serious illness.

Allergy alert:Acetaminophen may cause severe skin reactions. Symptoms may include:

- skin reddening
- blisters
- rash

If a skin reaction occurs, stop use and seek medical help right away.

Allergy alert:Aspirin may cause a severe allergic reaction which may include:

- hives
- facial swelling
- asthma (wheezing)
- shock

Liver warning:This product contains acetaminophen. Severe liver damage may occur if you take

- more than 2 caplets in 24 hours, which is the maximum daily amount
- with other drugs containing acetaminophen
- 3 or more alcoholic drinks every day while using this product

Stomach bleeding warning:This product contains an NSAID, which may cause severe stomach bleeding. The chance is higher if you

-
  - are age 60 or older
  - have had stomach ulcers or bleeding problems
  - take a blood thinning (anticoagulant) or steroid drug
  - take other drugs containing prescription or nonprescription NSAIDs (aspirin, ibuprofen, naproxen, or others)
  - have 3 or more alcoholic drinks every day while using this product
  - take more or for a longer time than directed

Medication overuse headache warning:Headaches may worsen if this product is used for 10 or more days per month.

Caffeine warning:The recommended dose of this product contains about as much caffeine as a cup of coffee. Limit the use of caffeine-containing medications, foods, or beverages while taking this product because too much caffeine may cause nervousness, irritability, sleeplessness, and, occasionally, rapid heart beat.

Do not use

-
  - if you have ever had an allergic reaction to acetaminophen, aspirin or any other pain reliever/fever reducer
  - with any other drug containing acetaminophen (prescription or nonprescription). If you are not sure whether a drug contains acetaminophen, ask a doctor or pharmacist.

Ask a doctor before use if

- you have never had migraines diagnosed by a health professional
  - you have a headache that is different from your usual migraines
  - you have the worst headache of your life
  - you have fever and stiff neck
  - you have headaches beginning after or caused by head injury, exertion, coughing or bending
  - you experienced your first headache after the age of 50
  - you have daily headaches
  - you have a migraine so severe as to require bed rest
  - you have liver disease
  - stomach bleeding warning applies to you
  - you have a history of stomach problems, such as heartburn
  - you have high blood pressure, heart disease, liver cirrhosis, or kidney disease
  - you are taking a diuretic
  - you have asthma
  - you have problems or serious side effects from taking pain relievers or fever reducers
  - you have vomiting with your migraine headache

Ask a doctor or pharmacist before use if you are

- taking a prescription drug for:
  - diabetes
  - gout
  - arthritis
  - under a doctor’s care for any serious condition
  - taking any other drug
  - taking any other product that contains aspirin, acetaminophen, or any other pain reliever/fever reducer

Stop use and ask a doctor if

- an allergic reaction occurs. Seek medical help right away.
- you experience any of the following signs of stomach bleeding:
  - feel faint
  - vomit blood
  - have bloody or black stools
  - have stomach pain that does not get better
  - your migraine is not relieved or worsens after first dose
  - new or unexpected symptoms occur
  - ringing in the ears or loss of hearing occurs

If pregnant or breast-feeding,

ask a health professional before use. It is especially important not to use aspirin at 20 weeks or later in pregnancy unless definitely directed to do so by a doctor because it may cause problems in the unborn child or complications during delivery.

Keep out of reach of children.

In case of overdose, get medical help or contact a Poison Control Center right away. Quick medical attention is critical for adults as well as for children even if you do not notice any signs or symptoms.

Directions

- do not use more than directed
- adults: take 2 caplets with a glass of water
- if symptoms persist or worsen, ask your doctor
- do not take more than 2 caplets in 24 hours, unless directed by a doctor
- under 18 years of age: ask a doctor

Other information

- store at controlled room temperature 20°-25°C (68°-77°F)
- close cap tightly after use
- read all product information before using. Keep this box for important information.

Inactive ingredients

benzoic acid, carnauba wax, FD&C blue no. 1, hypromellose, light mineral oil, low-substituted hydroxypropyl cellulose, microcrystalline cellulose, polysorbate 20, povidone, propylene glycol, simethicone, sorbitan monolaurate, stearic acid, titanium dioxide

Questions?

1-800-468-7746

PACKAGE LABEL

Excedrin

Migraine Relief

Acetaminophen 250mg, Aspirin 250mg (NSAID)

and Caffiene 65mg

Pain Reliever / Pain Reliever Aid

2Caplets Single-Pack